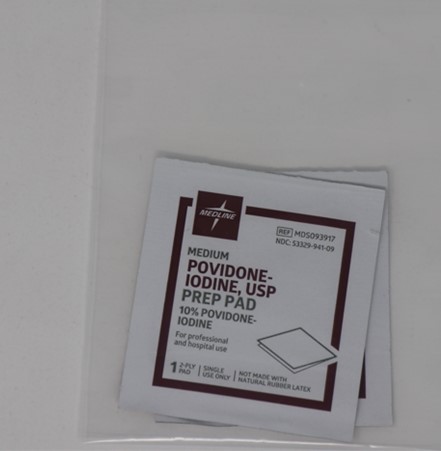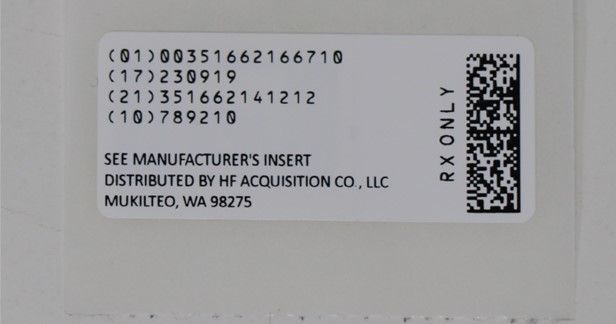 DRUG LABEL: POVIDONE-IODINE  PREP PADS MEDIUM
NDC: 51662-1667 | Form: CLOTH
Manufacturer: HF Acquisition Co. LLC, DBA HealthFirst
Category: otc | Type: HUMAN OTC DRUG LABEL
Date: 20250429

ACTIVE INGREDIENTS: POVIDONE-IODINE 10 mg/1 mL
INACTIVE INGREDIENTS: CITRIC ACID MONOHYDRATE; SODIUM PHOSPHATE, DIBASIC, ANHYDROUS; WATER

ACTIVE INGREDIENT

Povidone-Iodine, 10% w/w

PURPOSE

Antiseptic

USES

First aid antiseptic to help prevent infection in minor cuts, scrapes and burns

WARNINGS

For external use only.

Do not use

in the eyes
longer than 1 week unless directed by a physician
on individuals who are allergic or sensitive to iodine
or apply over large areas of the body

Stop use and ask a doctor if

irritation and redness develop
condition persists for more than 72 hours
in case of deep or puncture wounds, animal bites or serious burns

Keep out of reach of children.

If swallowed, get medical assistance or immediately contact a Poison Control Center.

Keep out of reach of children.

If swallowed, get medical assistance or immediately contact a Poison Control Center.

DIRECTIONS

clean the affected area
apply a small amount of this product on the area 1 to 3 times daily.
may be covered with a sterile bandage
if bandaged, let dry first

OTHER SAFETY INFORMATION

do not flush
protect from freezing, avoid excessive heat

INACTIVE INGREDIENT

citric acid, disodium phosphate, water

Stop use and ask a doctor if

irritation and redness develop
condition persists for more than 72 hours
in case of deep or puncture wounds, animal bites or serious burns

Stop use and ask a doctor if

irritation and redness develop
condition persists for more than 72 hours
in case of deep or puncture wounds, animal bites or serious burns

DOSAGE AND ADMINISTRATION

First aid antiseptic to help prevent infection in minor cuts, scrapes and burns

clean the affected area
apply a small amount of this product on the area 1 to 3 times daily.
may be covered with a sterile bandage
if bandaged, let dry first

INDICATIONS AND USAGE

clean the affected area
apply a small amount of this product on the area 1 to 3 times daily.
may be covered with a sterile bandage
if bandaged, let dry first